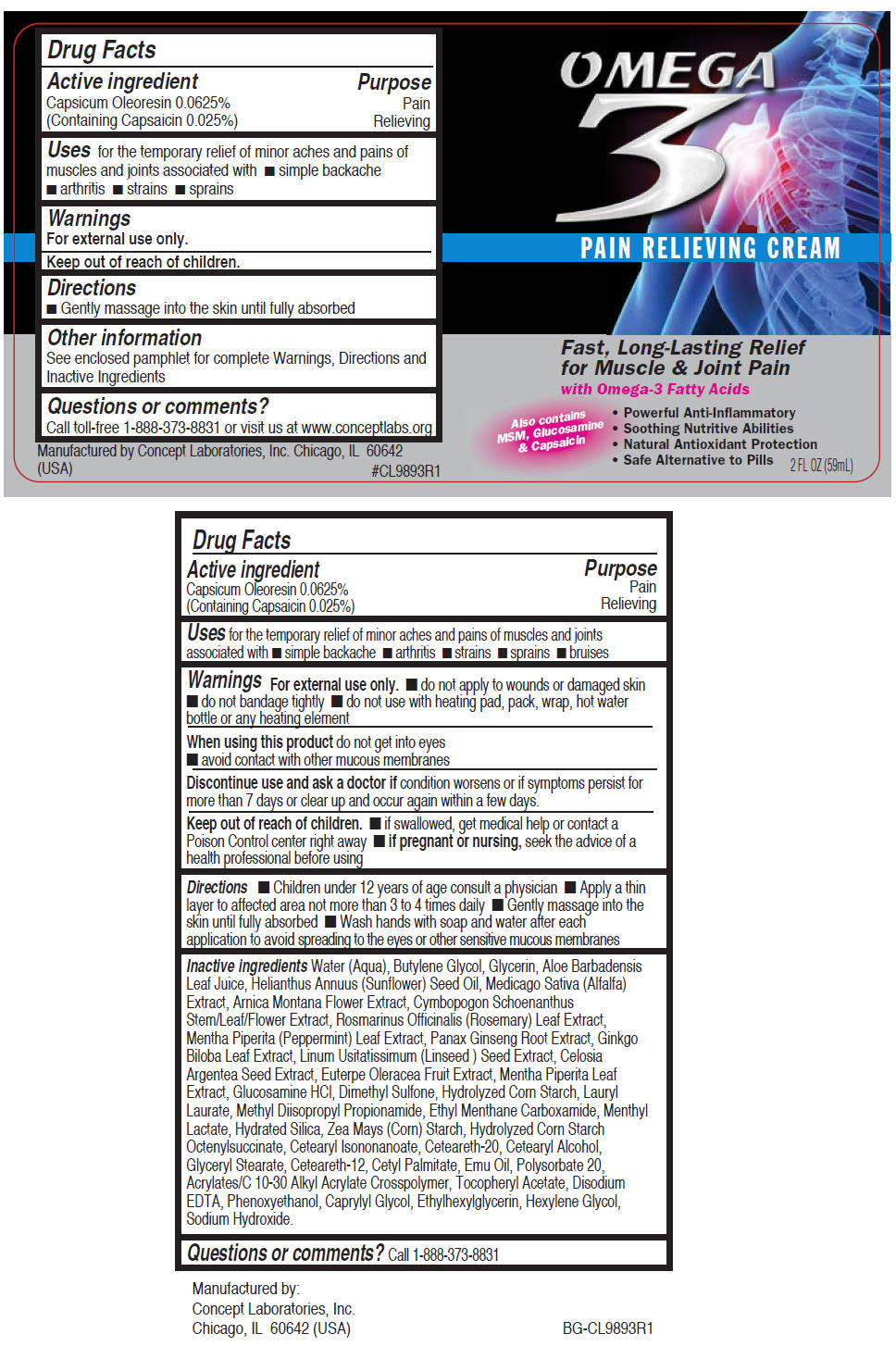 DRUG LABEL: Omega 3
NDC: 64058-353 | Form: CREAM
Manufacturer: Concept Laboratories, Inc.
Category: otc | Type: HUMAN OTC DRUG LABEL
Date: 20160915

ACTIVE INGREDIENTS: Capsaicin 2.5 mg/1 g
INACTIVE INGREDIENTS: Water; ALOE VERA LEAF; METHYL DIISOPROPYL PROPIONAMIDE; ETHYL MENTHANE CARBOXAMIDE; MENTHYL LACTATE, (-)-; LAURYL LAURATE; STARCH, CORN; HYDRATED SILICA; GLUCOSAMINE HYDROCHLORIDE; DIMETHYL SULFONE; GLYCERIN; SUNFLOWER OIL; ALFALFA; ARNICA MONTANA FLOWER; CYMBOPOGON SCHOENANTHUS TOP; ROSEMARY; MENTHA PIPERITA LEAF; ASIAN GINSENG; GINKGO; FLAX SEED; CELOSIA ARGENTEA SEED; ACAI; EDETATE DISODIUM; EMU OIL; POLYSORBATE 20; .ALPHA.-TOCOPHEROL ACETATE; BUTYLENE GLYCOL; PHENOXYETHANOL; CAPRYLYL GLYCOL; Ethylhexylglycerin; Hexylene Glycol; CETEARYL ISONONANOATE; POLYOXYL 20 CETOSTEARYL ETHER; CETOSTEARYL ALCOHOL; GLYCERYL MONOSTEARATE; CETEARETH-12; CETYL PALMITATE; SODIUM HYDROXIDE

Omega 3 Cream

Drug Facts

Active ingredient

Capsicum Oleoresin 0.0625% (Containing Capsaicin 0.025%)

Purpose

Pain Relieving

Uses

for the temporary relief of minor aches and pains of muscles and joints associated with

- simple backache
- arthritis
- strains
- sprains
- bruises

Warnings

For external use only.

- do not apply to wounds or damaged skin
- do not bandage tightly
- do not use with heating pad, pack, wrap, hot water bottle or any heating element

When using this product do not get into eyes

- avoid contact with other mucous membranes

STOP USE

Discontinue use and ask a doctor if condition worsens or if symptoms persist for more than 7 days or clear up and occur again within a few days.

Keep out of reach of children.

- if swallowed, get medical help or contact a Poison Control center right away

PREGNANCY OR BREAST FEEDING

- if pregnant or nursing, seek the advice of a health professional before using

Directions

- Children under 12 years of age consult a physician
- Apply a thin layer to affected area not more than 3 to 4 times daily
- Gently massage into the skin until fully absorbed
- Wash hands with soap and water after each application to avoid spreading to the eyes or other sensitive mucous membranes

Inactive ingredients

Water (Aqua), Butylene Glycol, Glycerin, Aloe Barbadensis Leaf Juice, Helianthus Annuus (Sunflower) Seed Oil, Medicago Sativa (Alfalfa) Extract, Arnica Montana Flower Extract, Cymbopogon Schoenanthus Stem/Leaf/Flower Extract, Rosmarinus Officinalis (Rosemary) Leaf Extract, Mentha Piperita (Peppermint) Leaf Extract, Panax Ginseng Root Extract, Ginkgo Biloba Leaf Extract, Linum Usitatissimum (Linseed) Seed Extract, Celosia Argentea Seed Extract, Euterpe Oleracea Fruit Extract, Mentha Piperita Leaf Extract, Glucosamine HCl, Dimethyl Sulfone, Hydrolyzed Corn Starch, Lauryl Laurate, Methyl Diisopropyl Propionamide, Ethyl Menthane Carboxamide, Menthyl Lactate, Hydrated Silica, Zea Mays (Corn) Starch, Hydrolyzed Corn Starch Octenylsuccinate, Cetearyl Isononanoate, Ceteareth-20, Cetearyl Alcohol, Glyceryl Stearate, Ceteareth-12, Cetyl Palmitate, Emu Oil, Polysorbate 20, Acrylates/C 10-30 Alkyl Acrylate Crosspolymer, Tocopheryl Acetate, Disodium EDTA, Phenoxyethanol, Caprylyl Glycol, Ethylhexylglycerin, Hexylene Glycol, Sodium Hydroxide.

Questions or comments?

Call 1-888-373-8831

Manufactured by:
Concept Laboratories, Inc.
Chicago, IL 60642 (USA)

PRINCIPAL DISPLAY PANEL - 59 mL Bottle Label

OMEGA
3

PAIN RELIEVING CREAM

Fast, Long-Lasting Relief
for Muscle & Joint Pain

with Omega-3 Fatty Acids

Also contains
MSM, Glucosamine
& Capsaicin

- Powerful Anti-Inflammatory
- Soothing Nutritive Abilities
- Natural Antioxidant Protection
- Safe Alternative to Pills

2 FL OZ (59mL)